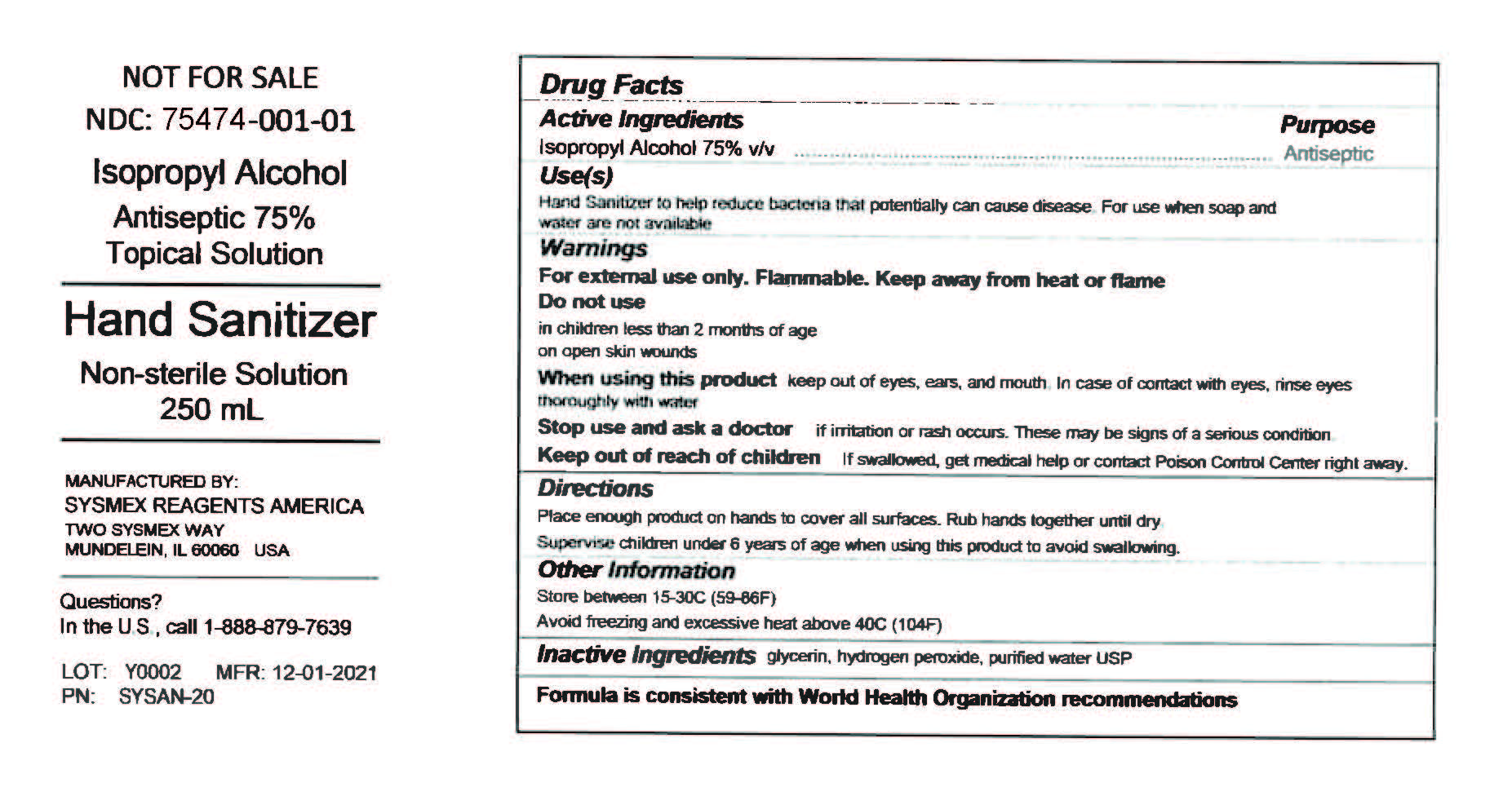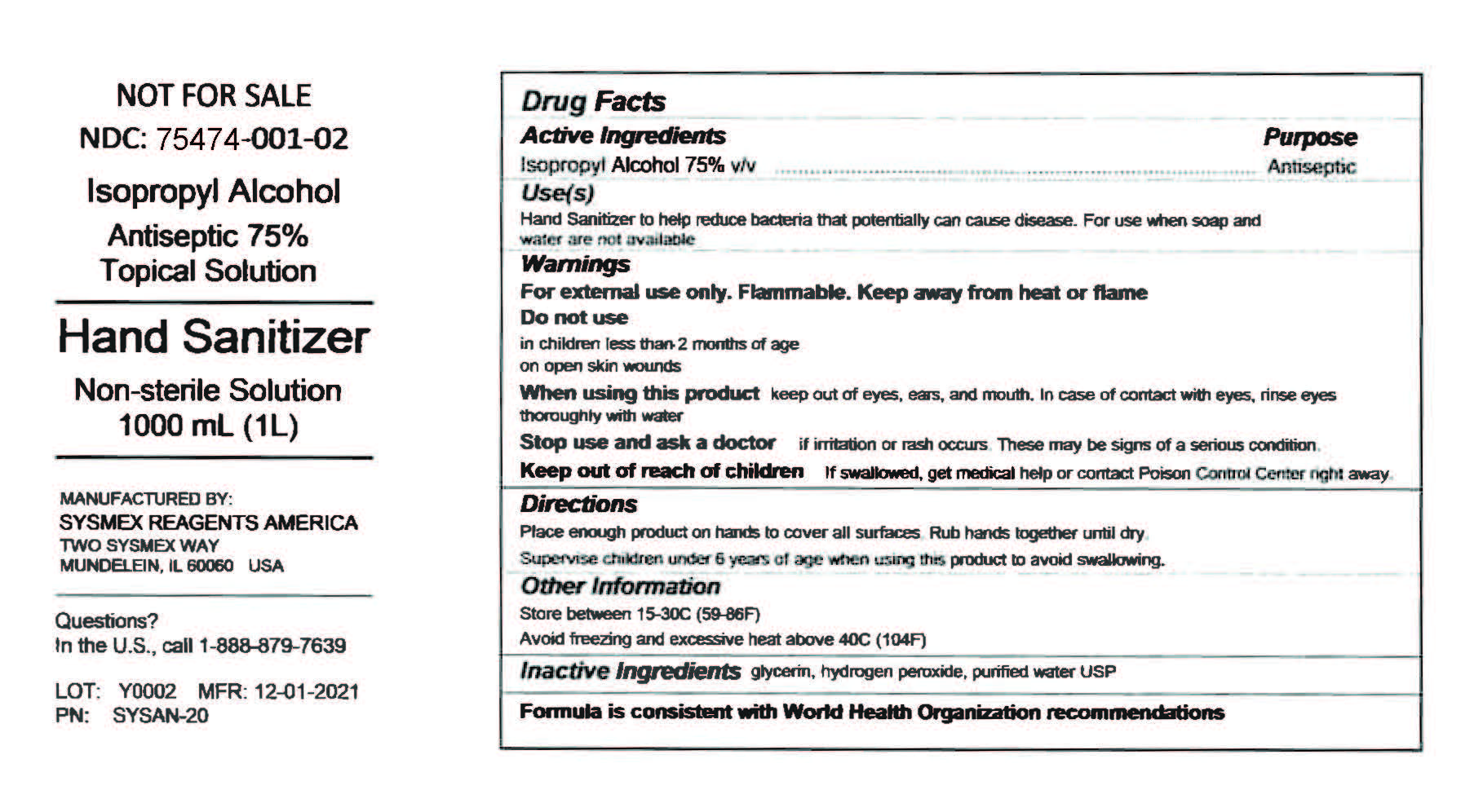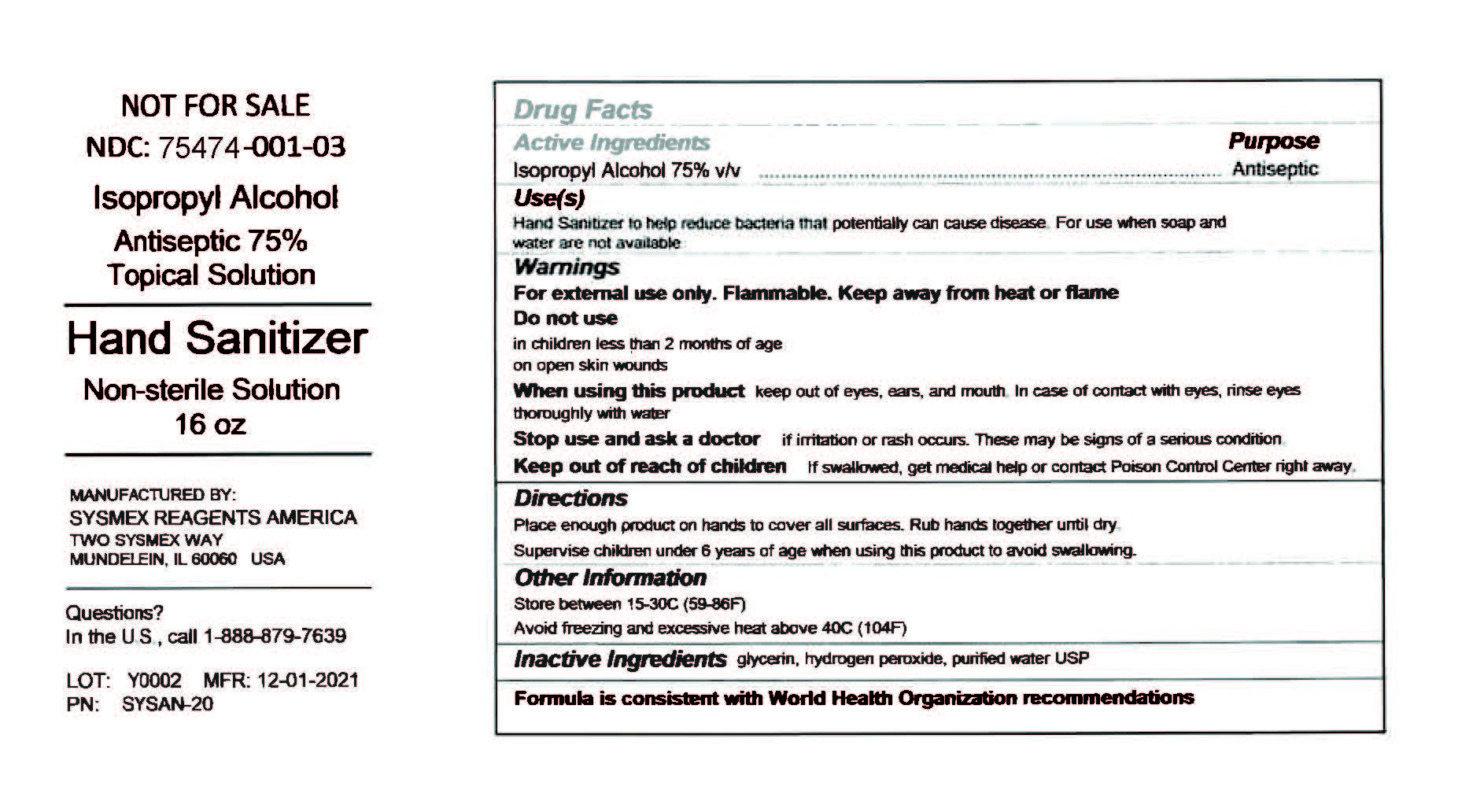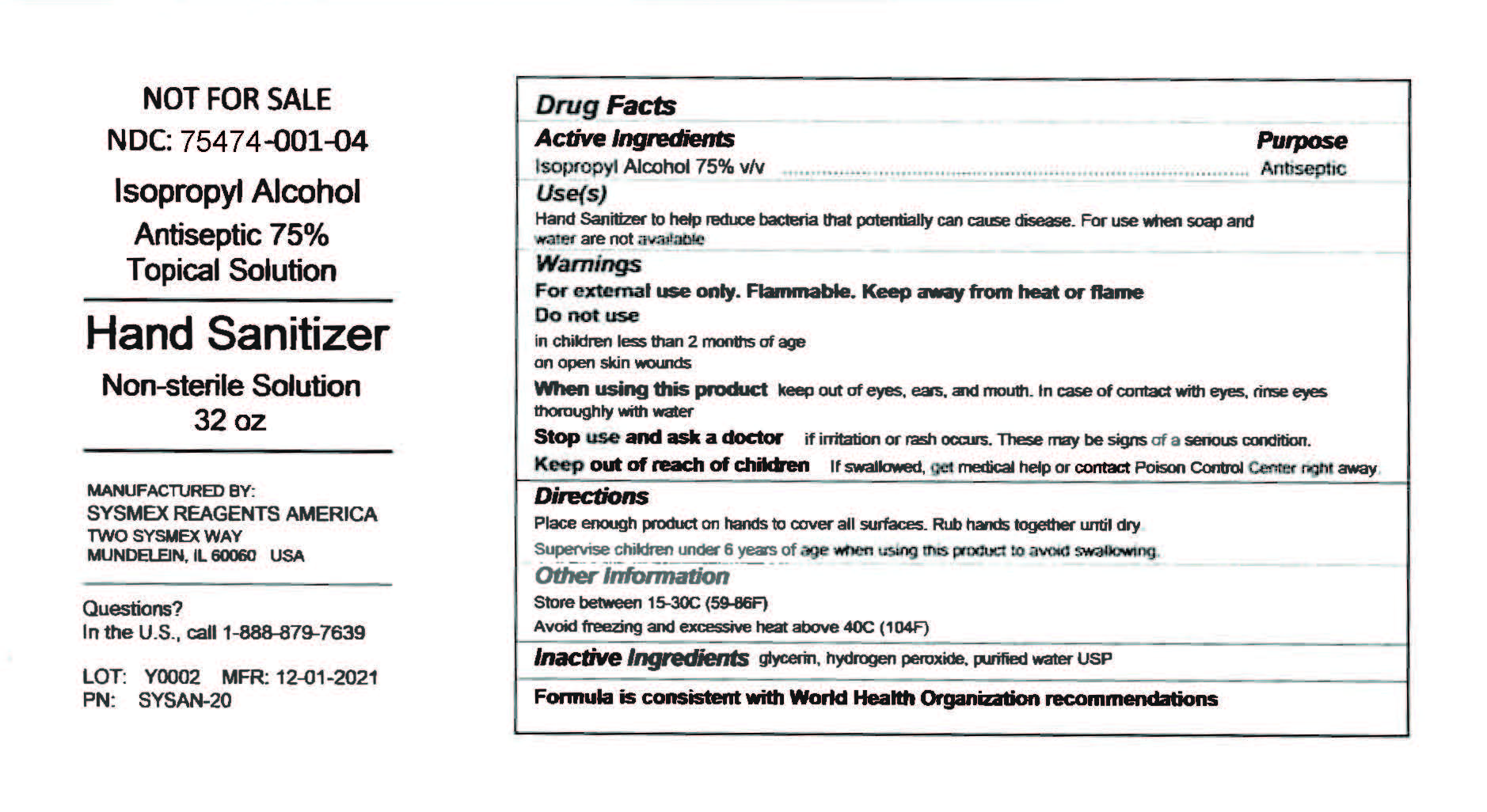 DRUG LABEL: 
                           
NDC: 75474-001 | Form: SOLUTION
Manufacturer: Sysmex Reagents America, Incorporated
Category: otc | Type: HUMAN OTC DRUG LABEL
Date: 20200411

ACTIVE INGREDIENTS: ALCOHOL 75 mL/100 mL
INACTIVE INGREDIENTS: GLYCERIN; Hydrogen Peroxide; Water

Hand Sanitizer
Non-sterile Solution

<This is a hand sanitizer manufactured according to the Temporary Policy for Preparation of Certain Alcohol-Based Hand Sanitizer Products During the Public Health Emergency (CoViD-19); Guidance for Industry.>

The hand sanitizer is manufactured using only the following United States Pharmacopoeia (USP) grade ingredients in the preparation of the product (percentage in final product formulation) consistent with World Health Organization (WHO) recommendations:

1. Isopropyl Alcohol (75%, v/v) in an aqueous solution denatured according to Alcohol and Tobacco Tax and Trade Bureau regulations in 27 CFR part 20.
2. Glycerol (1.45% v/v).
3. Hydrogen peroxide (0.125% v/v).
4. Sterile distilled water or boiled cold water.

The firm does not add other active or inactive ingredients. Different or additional ingredients may impact the quality and potency of the product.

<p class="First">This is a hand sanitizer manufactured according to the <a href="https://www.fda.gov/media/136289/download" data-mce-href="https://www.fda.gov/media/136289/download">Temporary Policy for Preparation of Certain Alcohol-Based Hand Sanitizer Products During the Public Health Emergency (CoViD-19); Guidance for Industry</a>.</p><p>The hand sanitizer is manufactured using only the following United States Pharmacopoeia (USP) grade ingredients in the preparation of the product (percentage in final product formulation) consistent with World Health Organization (WHO) recommendations:</p><ol class="LittleAlpha"><li>Isopropyl Alcohol (75%, v/v) in an aqueous solution denatured according to Alcohol and Tobacco Tax and Trade Bureau regulations in 27 CFR part 20.</li><li>Glycerol (1.45% v/v).</li><li>Hydrogen peroxide (0.125% v/v).</li><li>Sterile distilled water or boiled cold water.</li></ol><p>The firm does not add other active or inactive ingredients. Different or additional ingredients may impact the quality and potency of the product.</p>

Active Ingredient(s)

Isopropyl Alcohol 75% v/v. Purpose: Antiseptic

Purpose

Antiseptic, Hand Sanitizer

Use

Hand Sanitizer to help reduce bacteria that potentially can cause disease. For use when soap and water are not available.

Warnings

For external use only. Flammable. Keep away from heat or flame

Do not use

- in children less than 2 months of age
- on open skin wounds

When using this product keep out of eyes, ears, and mouth. In case of contact with eyes, rinse eyes thoroughly with water.
Stop use and ask a doctor if irritation or rash occurs. These may be signs of a serious condition.
Keep out of reach of children. If swallowed, get medical help or contact a Poison Control Center right away.

Stop use and ask a doctor if irritation or rash occurs. These may be signs of a serious condition.

Keep out of reach of children. If swallowed, get medical help or contact a Poison Control Center right away.

Directions

- Place enough product on hands to cover all surfaces. Rub hands together until dry.
- Supervise children under 6 years of age when using this product to avoid swallowing.

Other information

- Store between 15-30C (59-86F)
- Avoid freezing and excessive heat above 40C (104F)

Inactive ingredients

glycerin, hydrogen peroxide, purified water USP

Package Label - Principal Display Panel

250 mL NDC: 75474-001-01

Package Label - Principal Display Panel

1000 mL NDC: 75474-001-02

Package Label - Principal Display Panel

473.176 mL (16oz) NDC: 75474-001-03

Package Label - Principal Display Panel

946.35 mL (32oz) NDC: 75474-001-04